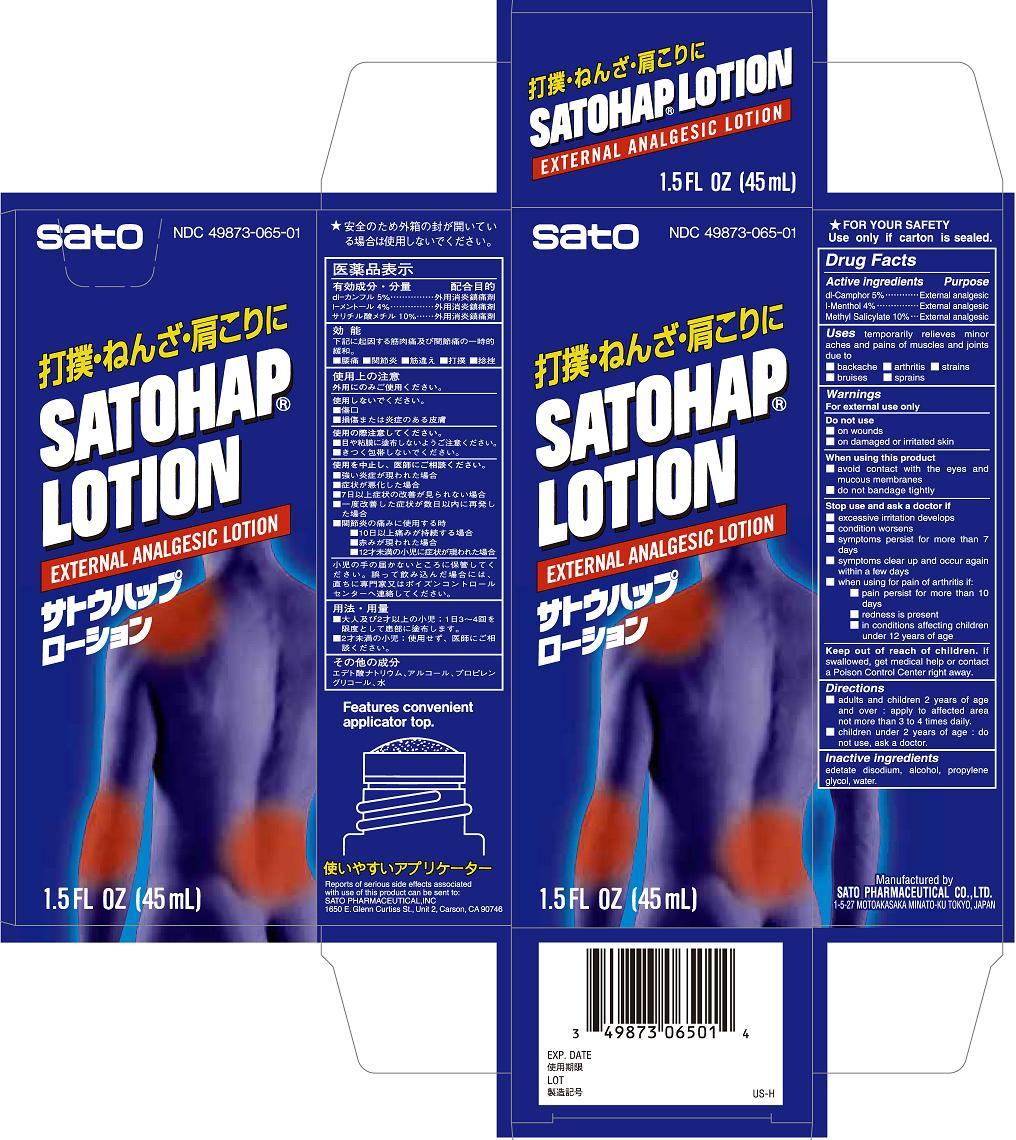 DRUG LABEL: Satohap
NDC: 49873-065 | Form: LOTION
Manufacturer: Sato Pharmaceutical Co., Ltd.
Category: otc | Type: HUMAN OTC DRUG LABEL
Date: 20231201

ACTIVE INGREDIENTS: METHYL SALICYLATE 10 g/100 mL; CAMPHOR (SYNTHETIC) 5 g/100 mL; LEVOMENTHOL 4 g/100 mL
INACTIVE INGREDIENTS: EDETATE DISODIUM; ALCOHOL; PROPYLENE GLYCOL; WATER

Satohap Lotion

Active ingredients
dl-Camphor 5%
l-Menthol 4%
Methyl salicylate 10%

Purpose
dl-Camphor External analgesic
l-Menthol External analgesic
Methyl salicylate External analgesic

Uses

temporarily relieves minor aches and pains of muscles and joints due to
■ backache ■ arthritis ■ strains ■ bruises ■ sprains

Warnings
For external use only

Do not use
■ on wounds
■ on damaged or irritated skin

When using this product
■ avoid contact with the eyes and mucous membranes
■ do not bandage tightly

Stop use and ask a doctor if
■ excessive irritation develops
■ condition worsens
■ symptoms persist for more than 7 days
■ symptoms clear up and occur again within a few days
■ when using for pain of arthritis if:
■ pain persist for more than 10 days
■ redness is present
■ in conditions affecting children under 12 years of age

Keep out of reach of children. If swallowed, get medical help or contact a Poison Control Center right away.

Directions
■ adults and children 2 years of age and over: apply to affected area not more than 3 to 4 times daily.
■ children under 2 years of age: do not use, ask a doctor.

Inactive ingredients
edetate disodium, alcohol, propylene glycol, water